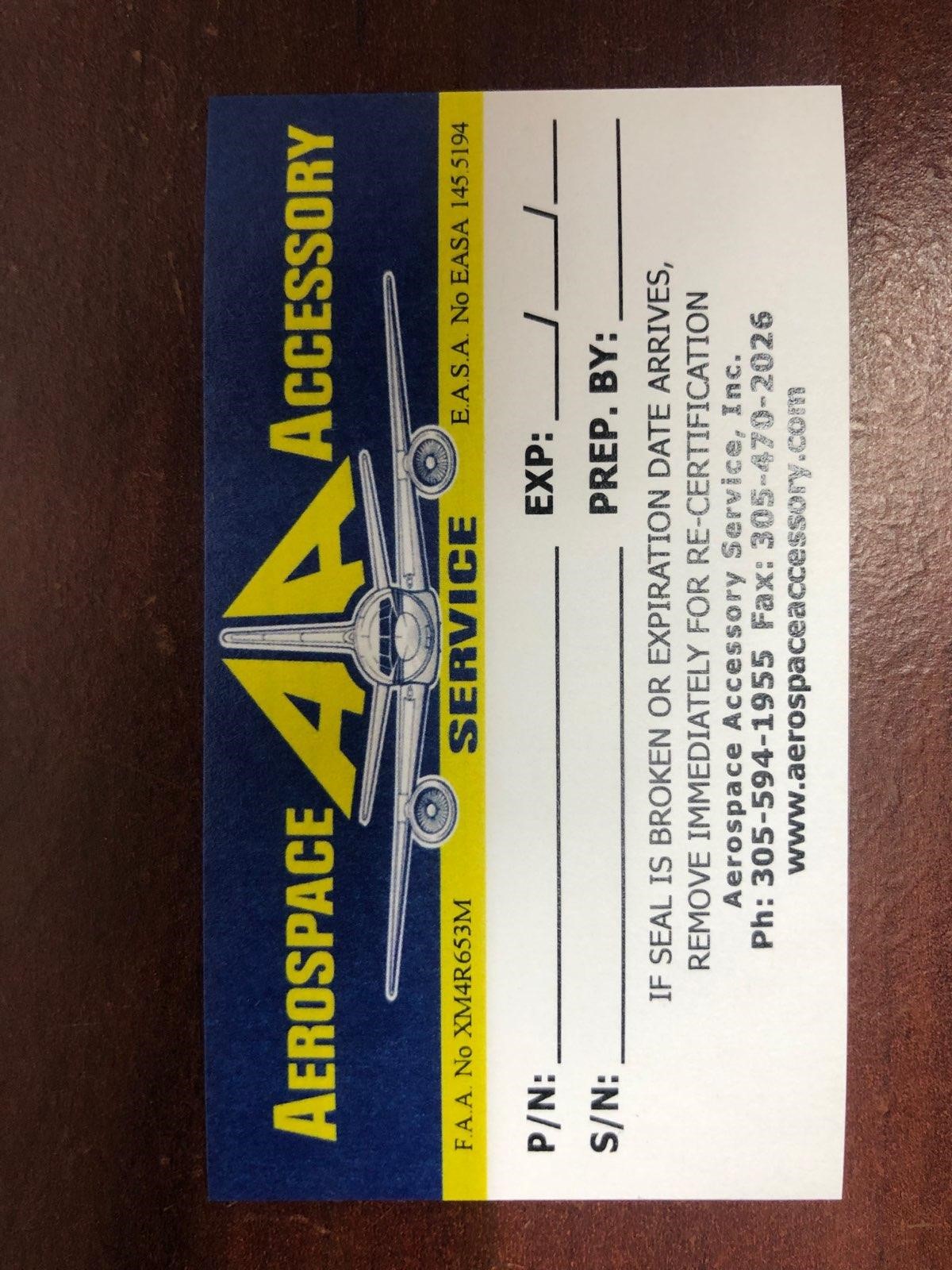 DRUG LABEL: Model AA-1218 Model AA-1218M Model Z-25-020-03
NDC: 27860-007 | Form: KIT | Route: TOPICAL
Manufacturer: Aerospace Accessory Service, Inc
Category: other | Type: MEDICAL DEVICE
Date: 20210505

ACTIVE INGREDIENTS: POVIDONE-IODINE 10 mg/1 mL; AMMONIA 0.045 g/0.3 mL; LIDOCAINE HYDROCHLORIDE 0.5 g/100 g; BENZALKONIUM CHLORIDE 0.13 g/100 g
INACTIVE INGREDIENTS: CITRIC ACID MONOHYDRATE; SODIUM PHOSPHATE, DIBASIC, ANHYDROUS; NONOXYNOL-9; SODIUM HYDROXIDE; WATER; ALCOHOL; FD&C RED NO. 40; WATER; ISOPROPYL MYRISTATE; METHYLCELLULOSE (25 MPA.S); CETOSTEARYL ALCOHOL; GLYCERYL MONOSTEARATE; DIMETHICONE; CETETH-20; BUTYLATED HYDROXYTOLUENE; METHYLPARABEN SODIUM; PROPYLPARABEN SODIUM; GLYCERIN; EDETATE SODIUM; WATER

Model AA-1218
Model AA-1218M
Model Z-25-020-03

Aerospace Accessory Service

P/N:

S/N:

EXP:

Prep. By: